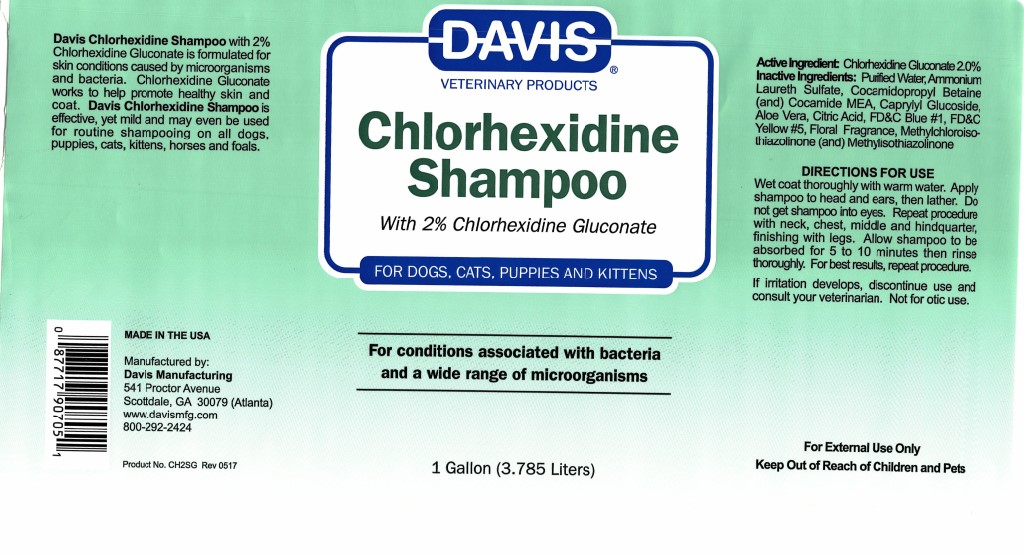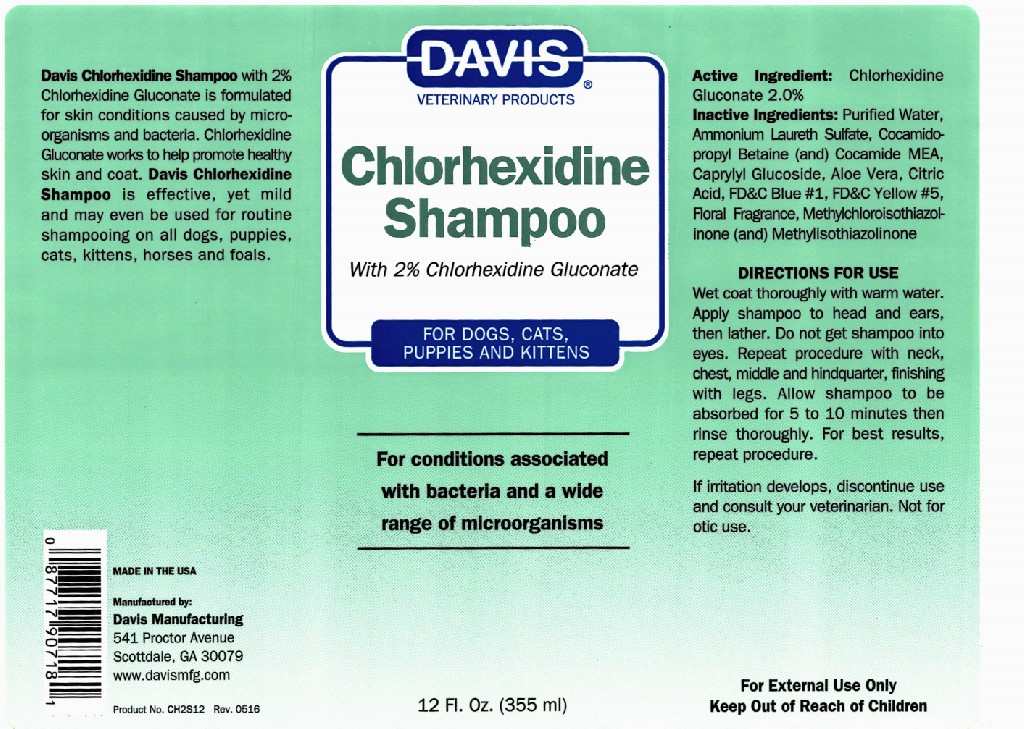 DRUG LABEL: Davis Chlorhexidine
NDC: 62570-023 | Form: SHAMPOO
Manufacturer: Davis Manufacturing and Packaging Inc
Category: animal | Type: OTC ANIMAL DRUG LABEL
Date: 20191105

ACTIVE INGREDIENTS: CHLORHEXIDINE GLUCONATE 2 g/100 g
INACTIVE INGREDIENTS: POLY(LAURYLGLUCOSIDE)-7; COCO MONOETHANOLAMIDE; COCAMIDOPROPYL BETAINE; SODIUM CHLORIDE; ALOE VERA LEAF; FD&C BLUE NO. 1; FD&C YELLOW NO. 5; AMMONIUM LAURYL SULFATE

Davis Chlorhexidine Shampoo 2%

DESCRIPTION

Davis Chlorhexidine Shampoo with 2% Chlorhexidine Gluconate is for skin conditions caused by microorganisms and bacteria. Chlorhexidine Gluconate works to help promote healthy skin and coat. Davis Chlorhexidine Shampoo is effective, yet mild and may even be used for routine shampooing on all dogs, puppies, cats, kittens, horses and foals.

MADE IN THE USA

Manufactured by: Davis Manufacturing 541 Proctor Avenue Scottdale, GA 30079

www.davismfg.com

Active Ingredients: Chlorhexidine Gluconate 2.0%

INACTIVE INGREDIENT

Inactive Ingredients: Purified water, Ammonium Lureth Sulfate, Cocamidopropyl Betaine (and) Cocamide MEA, caprylyl Glucoside, Aloe Vera, Citric Acid, FD&C Blue #1, FD&C Yellow #5, Floral Fragrance, Methylchloroisothiazolinone (and) Methylisothaiazolinone

Directions for use
Wet coat thoroughly with warm water. Apply shampoo to head and ears, then lather. Do not get shampoo into eyes. Repeat procedure with neck, chest, middle and hindquarters, finishing with legs. Allow shampoo to be absorbs for 5 to 10 minutes then rinse thoroughly. For best results repeat procedure.

PRECAUTIONS

If irritaion develops, discontinue use and consult your veterinarian. Not for otic use.

For External use only

Keep out of reach of children and pets

Principal Display Panel 12 oz (355 ml)

Davis

VETERINARY PRODUCTS

Chlorhexidine Shampoo

with 2% Chlorhexidine Gluconate

For Dogs, Cats, Puppies, and Kittens

For Conditions Associated with bacteria and a wide range of microorganisms

12 Fl. Oz. (355 ml)

Principal Display Panel 1 Gallon

Davis

VETERINARY PRODUCTS

Chlorhexidine Shampoo

with 2% Chlorhexidine Gluconate

For Dogs, Cats, Puppies, and Kittens

For Conditions Associated with bacteria and a wide range of microorganisms

1 Gallon (3.785 Liters)